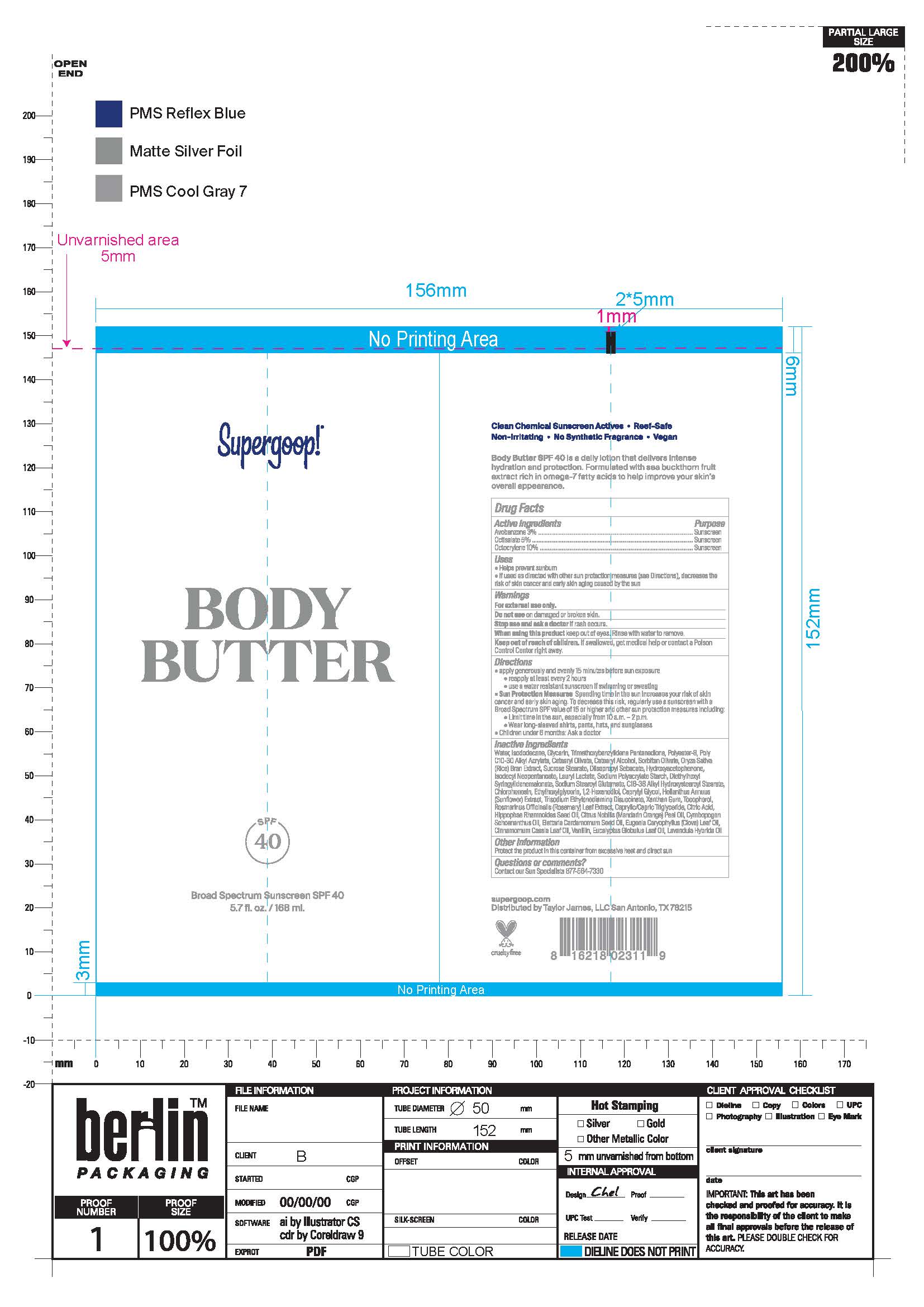 DRUG LABEL: Body Butter Broad Spectrum Sunscreen SPF 40
NDC: 75936-256 | Form: CREAM
Manufacturer: Taylor James Ltd.
Category: otc | Type: HUMAN OTC DRUG LABEL
Date: 20211011

ACTIVE INGREDIENTS: AVOBENZONE 3 g/100 mL; OCTISALATE 5 g/100 mL; OCTOCRYLENE 10 g/100 mL
INACTIVE INGREDIENTS: WATER; ISODODECANE; GLYCERIN; TRIMETHOXYBENZYLIDENE PENTANEDIONE; POLYESTER-8 (1400 MW, CYANODIPHENYLPROPENOYL CAPPED); CETEARYL OLIVATE; CETOSTEARYL ALCOHOL; SORBITAN OLIVATE; RICE BRAN; SUCROSE STEARATE; DIISOPROPYL SEBACATE; HYDROXYACETOPHENONE; ISODECYL NEOPENTANOATE; LAURYL LACTATE; DIETHYLHEXYL SYRINGYLIDENEMALONATE; SODIUM STEAROYL GLUTAMATE; CHLORPHENESIN; ETHYLHEXYLGLYCERIN; 1,2-HEXANEDIOL; CAPRYLYL GLYCOL; HELIANTHUS ANNUUS FLOWERING TOP; TRISODIUM ETHYLENEDIAMINE DISUCCINATE; XANTHAN GUM; TOCOPHEROL; ROSEMARY; MEDIUM-CHAIN TRIGLYCERIDES; CITRIC ACID MONOHYDRATE; HIPPOPHAE RHAMNOIDES SEED OIL; MANDARIN OIL; CYMBOPOGON SCHOENANTHUS OIL; CARDAMOM OIL; CLOVE LEAF OIL; CHINESE CINNAMON LEAF OIL; VANILLIN; EUCALYPTUS OIL; LAVANDIN OIL

Body Butter SPF 40

Active Ingredients Purpose

Avobenzone 3% Sunscreen

Octisalate 5% Suncreen

Octocrylene 10% Sunscreen

Uses

• Helps Prevent Sunburn
• If used as directed with other sun protection measures (see Directions), decreases the risk of skin cancer and early skin aging caused by the sun.

Keep out of reach of children
If swallowed, get medical help or contact a poison Control Center right away

Stop use and ask a doctor if rash occurs

Warnings

- For external use only

- Do not use on damaged or broken skin
- When using this product keep out of eyes. Rinse with water to remove

Directions

- Apply generously and evenly 15 minutes before sun exposure
- Reapply at least every 2 hours.
- Use a water-resistant sunscreen if swimming or sweating

• Sun Protection Measures Spending time in the sun increases your risk of
skin cancer and early skin aging. To decrease this risk, regularly use a
sunscreen with a Broad-Spectrum SPF value of 15 or higher and other sun
protection measures including: • limit your time in the sun, especially from 10
a.m. – 2 p.m. • wear long-sleeved shirts, pants, hats, and sunglasses •
• Children under 6 months of age: ask a doctor.

Inactive Ingredients

Water, Isododecane, Glycerin, Trimethoxybenzylidene Pentanedione, Polyester-8, Poly C10-30 Alkyl Acrylate, Cetearyl Olivate, Oryza Sativa (Rice) Bran Extract, Sucrose Stearate, Diisopropyl Sebacate, Hydroxyacetophenone, Isodecyl Neopentanoate, Lauryl Lactate, Sodium Polyacrylate Starch, Diethylhexyl Syringlidenemalonate, Sodium Stearoyl Glutamate, C18-38 Alkyl Hydroxystearoyl Stearate, Chlorphenesin, Ethylhexylglycerin, 1,2 Hexanediol, Caprylyl Glycol, Helianthus Annuus(Sunflower) Extract, Trisodium Ethylenediamine Disuccinate, Xanthan Gum, Tocopherol, Romarinus Officinialis (Rosemary) Leaf Extract, Caprylic/Capric Triglyceride, Citric Acid, Hippophae Rhamnoides Seed Oil, Citrus Nobilis (Manadarin Orange) Peel Oil, Cymbopogon Schoenanthus Oil, Elettaria Cardamomum Seed Oil, Eugenia Caryophyllus (Clove) Leaf Oil, Cinnamomum Cassia, Vanillin, Eucalyptus Globulus Leaf Oil, Lavandula Hybrida Oil

PACKAGE LABEL

Supergoop!

Body Butter

SPF 40

Broad Spectrum Sunscreen SPF 40

5.7 fl. oz./168 ml